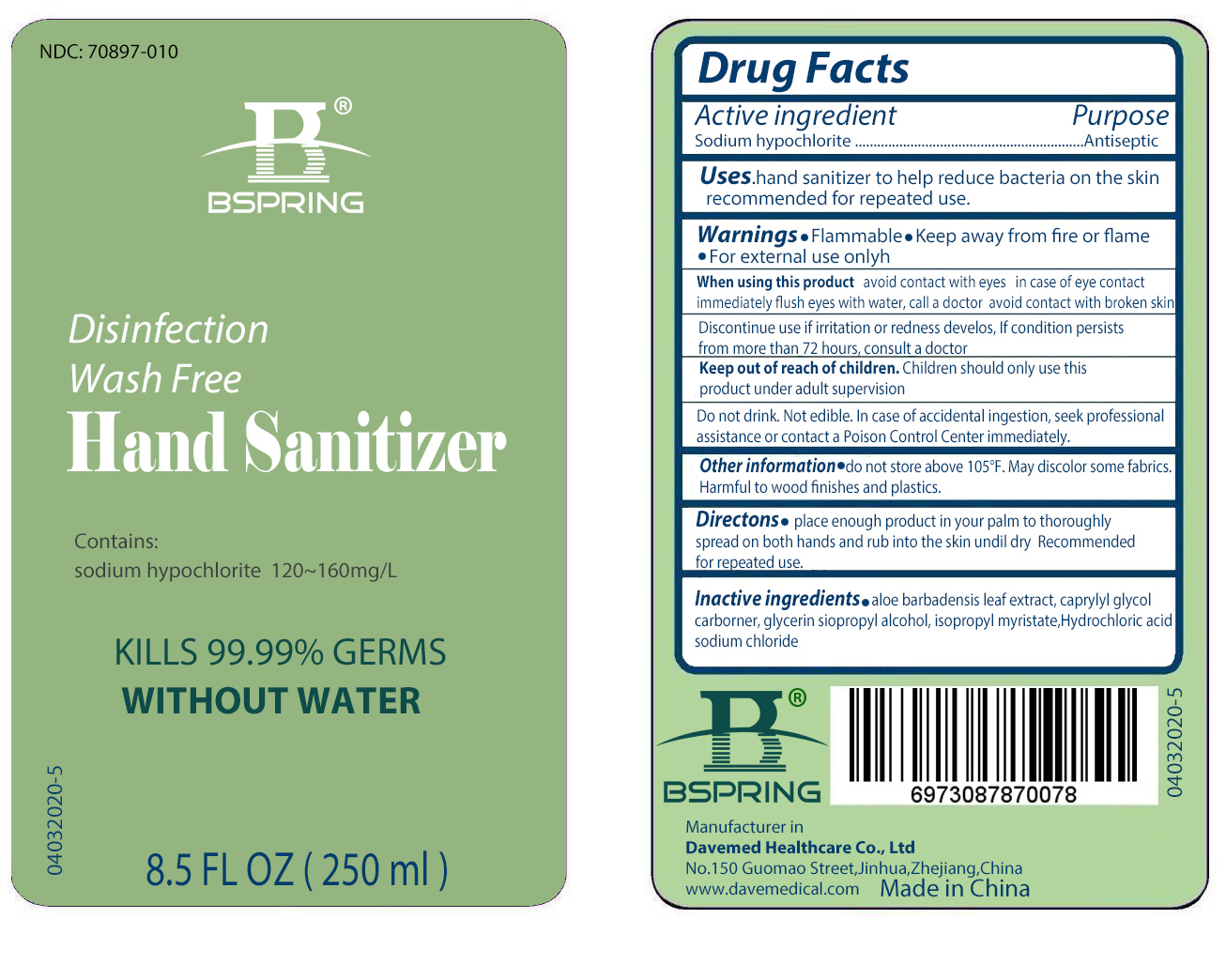 DRUG LABEL: Disinfection Wash Free Hand Sanitizer
NDC: 70897-010 | Form: LIQUID
Manufacturer: Davemed Healthcare Co., Ltd.
Category: otc | Type: HUMAN OTC DRUG LABEL
Date: 20200402

ACTIVE INGREDIENTS: SODIUM HYPOCHLORITE 120 mg/1000 mL
INACTIVE INGREDIENTS: CARBOMER HOMOPOLYMER, UNSPECIFIED TYPE; ISOPROPYL MYRISTATE; CAPRYLYL GLYCOL; ISOPROPYL ALCOHOL; GLYCERIN; ALOE VERA LEAF; HYDROCHLORIC ACID; SODIUM CHLORIDE

Disinfection Wash Free Hand Sanitizer

Active ingredient

Sodium hypochlorite

Purpose

Antiseptic

Uses

Hand sanitizer to help reduce bacteria on the skin recommended for repeated use.

Warnings

- Flammable
- Keep away from fire or flame
- For external use only

When using this product

- avoid contact with eyes in case of eye contact immediately flush eyes with water, call a doctor
- avoid contact with broken skin
- Discontinue use if irritation or redness develops. If condition persists from more than 72 hours, consult a doctor

Keep out of reach of children. Children should only use this product unde adult supervision. Do not drink. Not edible. In case of accidental ingestion, seek professional assistance or contact a Poison Control Center immediately.

Other information

- Do not store above 150F.
- May discolor some fabrics
- Harmful to wood finishes and plastics

Directions

- Place enough product in your palm to thoroughly spread on both hands and rub into the skin until dry. Recommended for repeated use.

Inactive ingredients

aloe barbadensis leaf extract, caprylyl glycol, carbomer, glycerin siopropyl alcohol, isopropyl alcohol myristate, Hyrochloric acid, sodium chloride